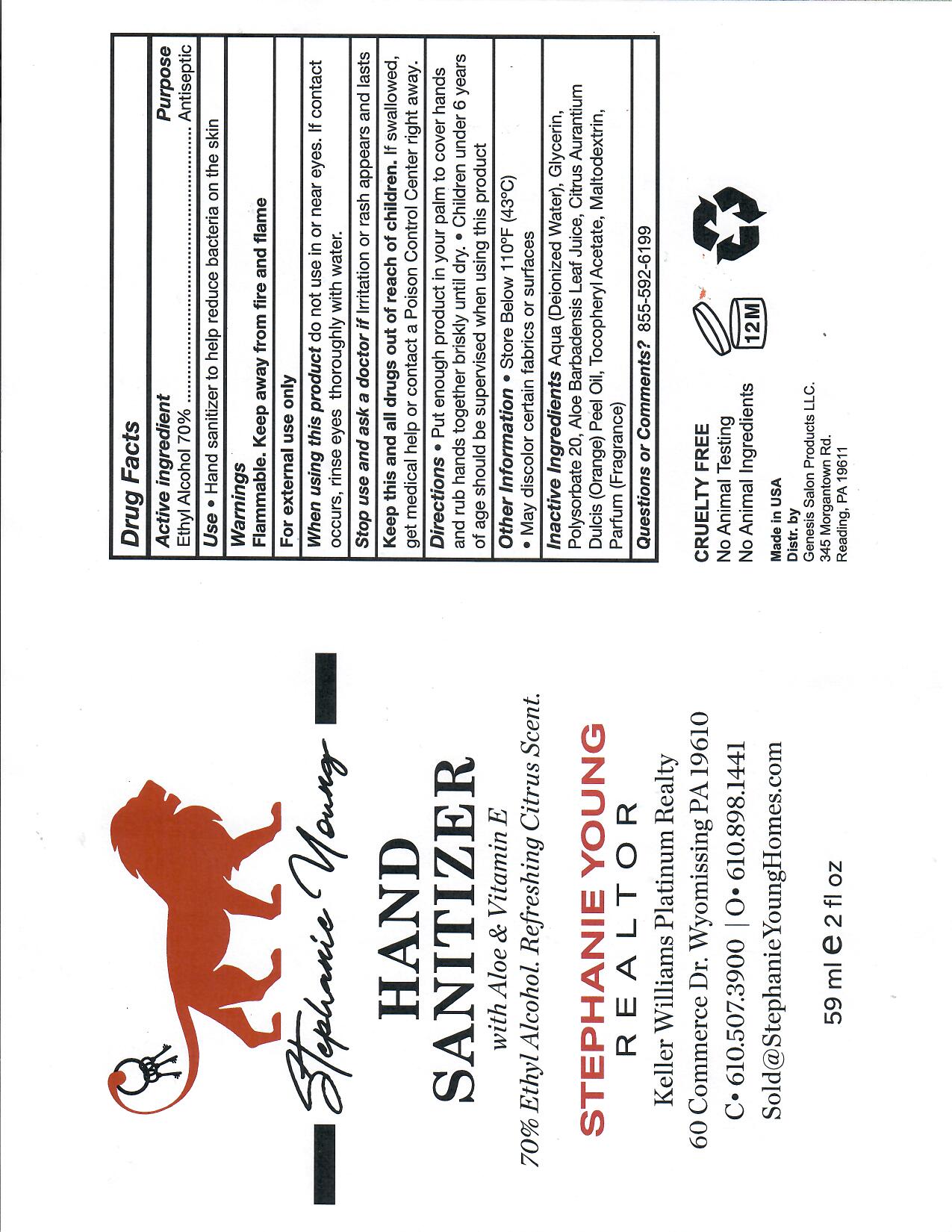 DRUG LABEL: HandSanitizerStephanieYoung
NDC: 76650-122 | Form: SOLUTION
Manufacturer: Genesis Salon Products
Category: otc | Type: HUMAN OTC DRUG LABEL
Date: 20201009

ACTIVE INGREDIENTS: ALCOHOL 70 mL/100 mL
INACTIVE INGREDIENTS: GLYCERIN; POLYSORBATE 20; WATER; ALOE; orange peel

This is a hand rub manufactured according to the Temporary Policy for Preparation of Certain Alcohol-Based Hand Rub Products During the Public Health Emergency (CoViD-19); Guidance for Industry.

The hand rub is manufactured using only the following United States Pharmacopoeia (USP) grade ingredients in the preparation of the product (percentage in final product formulation) consistent with World Health Organization (WHO) recommendations:

1. Alcohol (ethanol)
2. Glycerol
3. Sterile distilled water.

Active Ingredient(s)

Alcohol 70% Purpose: Antiseptic

Purpose

Antiseptic, Hand Rub

Use

Hand Sanitizerto help reduce bacteria on the skin

Warnings

Flammable. Keep away from heat or flame

Do not use

- in or around eyes

When using this product do not use in or near eyes. If contact occurs, rinse eyes thoroughly with water.

Stop use and ask a doctor if irritation or rash appears and lasts.

KEEP OUT OF REACH OF CHILDREN

Keep this and all drugs out of reach of children. If swallowed, get medical help or contact Poison Control Center right away.

Directions

- Put enough product in your palm to cover hands and rub together briskly until dry.
- Children under 6 years of age shoud be supervised when using this product.

Other information

- Store below 110F (43C)
- May discolor certain fabrics or surfaces

Inactive ingredients

Deionized water, glycerin, polysorbate 20, aloe barbadensis leaf juice, orange peel oil, tocopheryl acetate, maltodextrin, parfum